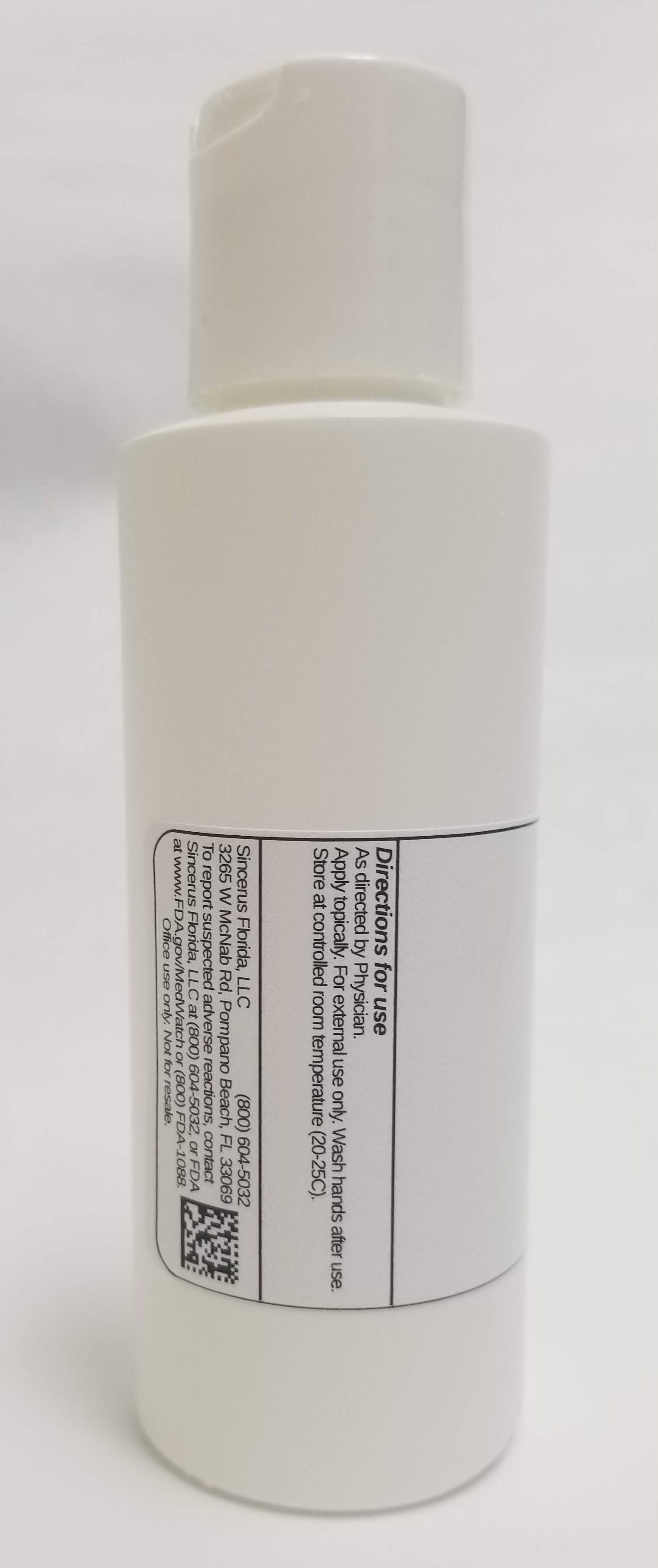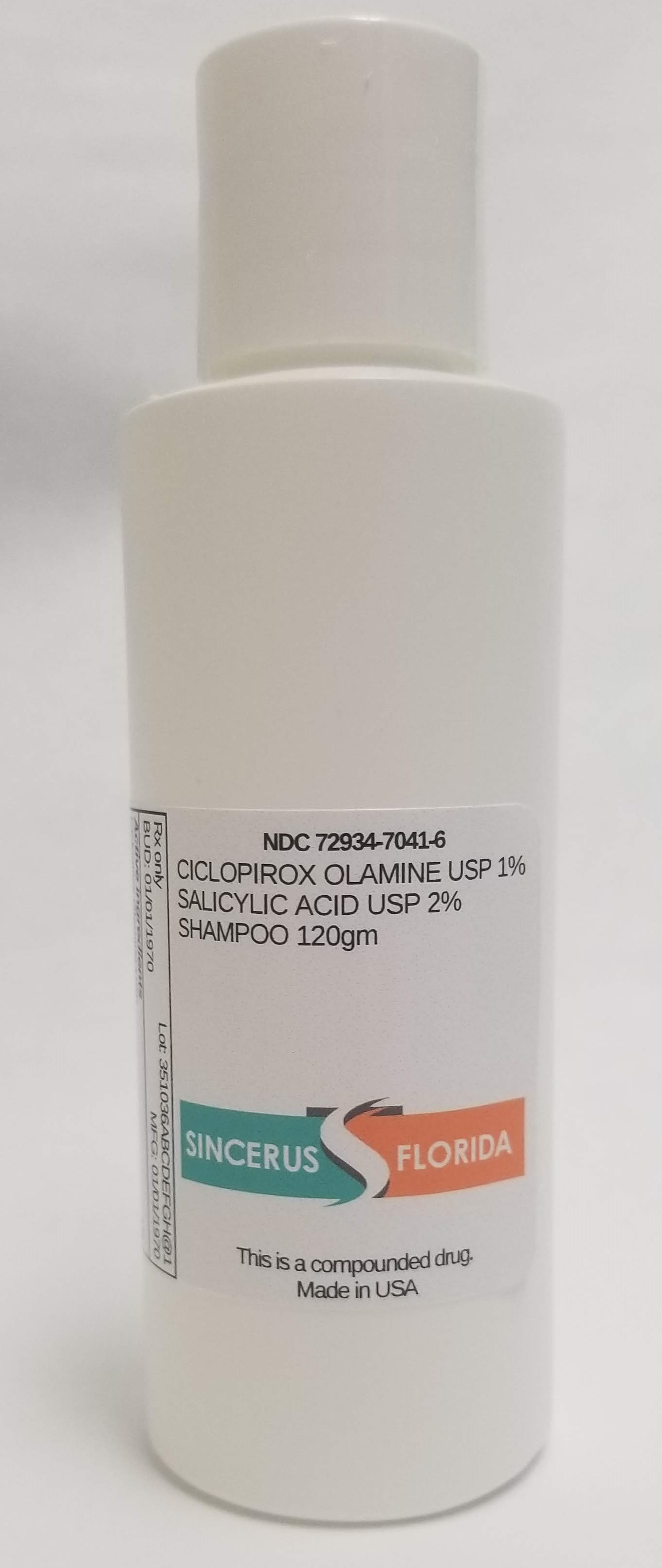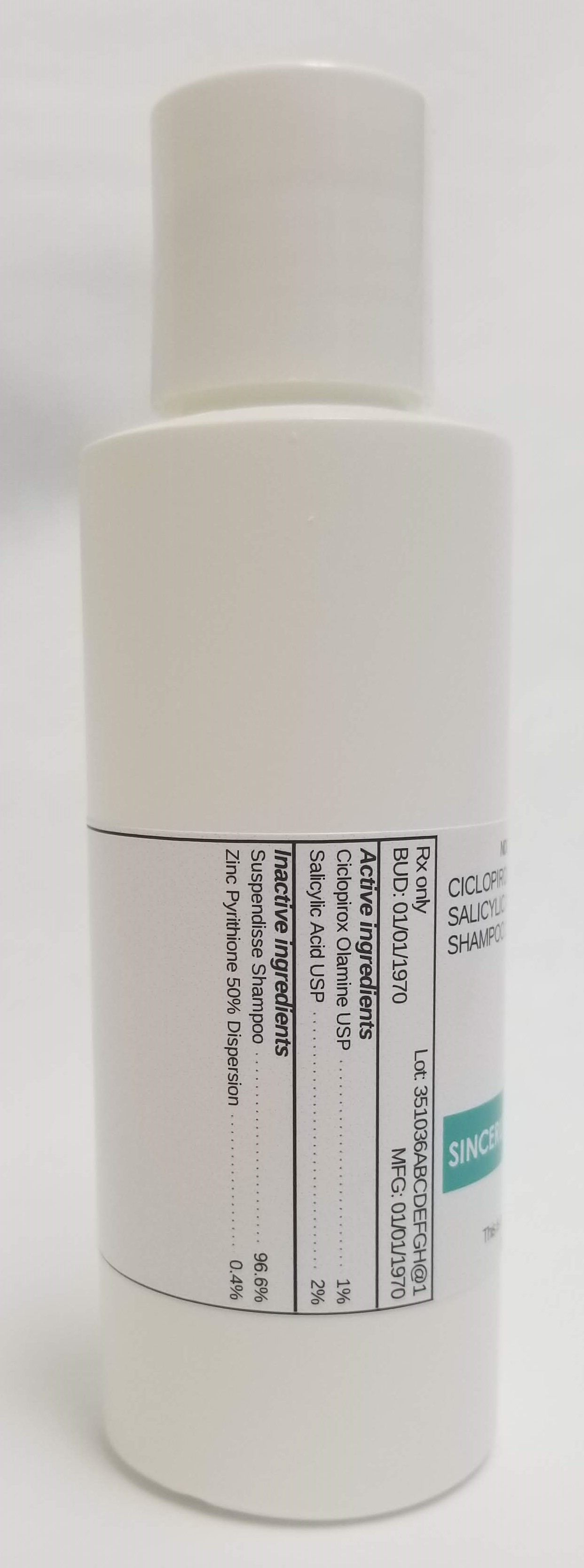 DRUG LABEL: CICLOPIROX OLAMINE 1% / SALICYLIC ACID 2%
NDC: 72934-7041 | Form: SHAMPOO
Manufacturer: Sincerus Florida, LLC
Category: prescription | Type: HUMAN PRESCRIPTION DRUG LABEL
Date: 20190522

ACTIVE INGREDIENTS: CICLOPIROX OLAMINE 1 g/100 g; SALICYLIC ACID 2 g/100 g

CICLOPIROX 1% / SALICYLIC ACID 2%